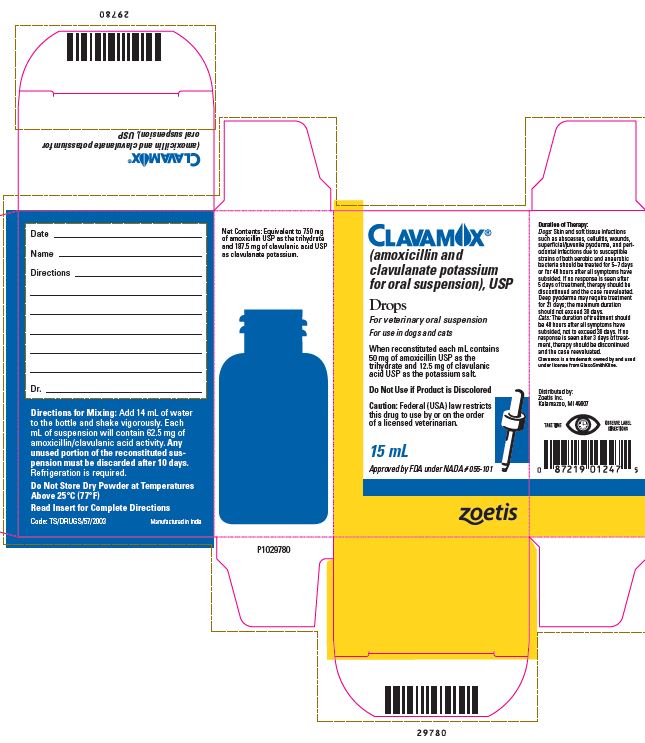 DRUG LABEL: Clavamox
NDC: 54771-6064 | Form: SUSPENSION
Manufacturer: Zoetis Inc.
Category: animal | Type: PRESCRIPTION ANIMAL DRUG LABEL
Date: 20241114

ACTIVE INGREDIENTS: AMOXICILLIN 50 mg/1 mL; CLAVULANATE POTASSIUM 12.5 mg/1 mL

CLAVAMOX® Drops

CLAVAMOX®
(amoxicillin and clavulanate potassium for oral suspension), USP
Drops

For veterinary oral suspension

For use in dogs and cats

CAUTION

Federal (USA) law restricts this drug to use by or on the order of a licensed veterinarian.

DESCRIPTION

Clavamox (amoxicillin trihydrate/clavulanate potassium), USP is an orally administered formulation comprised of the broad-spectrum antibiotic Amoxi® (amoxicillin trihydrate) and the β-lactamase inhibitor, clavulanate potassium (the potassium salt of clavulanic acid).

Amoxicillin trihydrate is a semisynthetic antibiotic with a broad spectrum of bactericidal activity against many gram-positive and gram-negative, aerobic and anaerobic microorganisms. It does not resist destruction by β-lactamases; therefore, it is not effective against β-lactamase-producing bacteria. Chemically, it is D(-)-α-amino-p-hydroxybenzyl penicillin trihydrate.

Clavulanic acid, an inhibitor of β-lactamase enzymes, is produced by the fermentation of Streptomyces clavuligerus. Clavulanic acid by itself has only weak antibacterial activity. Chemically, clavulanate potassium is potassium z-(3R,5R)-2-β-hydroxyethylidene clavam-3-carboxylate.

CLINICAL PHARMACOLOGY

Clavamox is stable in the presence of gastric acid and is not significantly influenced by gastric or intestinal contents. The 2 components are rapidly absorbed resulting in amoxicillin and clavulanic acid concentrations in serum, urine, and tissues similar to those produced when each is administered alone.

Amoxicillin and clavulanic acid diffuse readily into most body tissues and fluids with the exception of brain and spinal fluid, which amoxicillin penetrates adequately when meninges are inflamed. Most of the amoxicillin is excreted unchanged in the urine. Clavulanic acid's penetration into spinal fluid is unknown at this time. Approximately 15% of the administered dose of clavulanic acid is excreted in the urine within the first 6 hours.

Clavamox combines the distinctive properties of a broad-spectrum antibiotic and a β-lactamase inhibitor to effectively extend the antibacterial spectrum of amoxicillin to include β-lactamase-producing as well as non-β-lactamase-producing aerobic and anaerobic organisms.

Microbiology

Amoxicillin is bactericidal in action and acts through the inhibition of biosynthesis of cell wall mucopeptide of susceptible organisms. The action of clavulanic acid extends the antimicrobial spectrum of amoxicillin to include organisms resistant to amoxicillin and other β-lactam antibiotics.

Amoxicillin/clavulanate has been shown to have a wide range of activity which includes β-lactamaseproducing strains of both gram-positive and gram-negative aerobes, facultative anaerobes, and obligate anaerobes. Many strains of the following organisms, including β-lactamase-producing strains, isolated from veterinary sources, were found to be susceptible to amoxicillin/clavulanate in vitro but the clinical significance of this activity has not been demonstrated for some of these organisms in animals. Aerobic bacteria, including Staphylococcus aureus*, β-lactamase-producing Staphylococcus aureus* (penicillin resistant), Staphylococcus species*, Staphylococcus epidermidis, Staphylococcus intermedius, Streptococcus faecalis, Streptococcus species*, Corynebacteriumpyogenes, Corynebacterium species, Erysipelothrix rhusiopathiae, Bordetella bronchiseptica, Escherichia coli*, Proteus mirabilis, Proteus species, Enterobacter species, Klebsiellapneumoniae, Salmonelladublin, Salmonellatyphimurium, Pasteurellamultocida*, Pasteurellahaemolytica, Pasteurella species*.

* The susceptibility of these organisms has also been demonstrated in in vivo studies.

Studies have demonstrated that both aerobic and anaerobic flora are isolated from gingival cultures of dogs with clinical evidence of periodontal disease. Both gram-positive and gram-negative aerobic and anaerobic subgingival isolates indicate sensitivity to amoxicillin/clavulanic acid during antimicrobial susceptibility testing.

Susceptibility test

The recommended quantitative disc susceptibility method (FEDERAL REGISTER 37:20527–29; Bauer AW, Kirby WMM, Sherris JC, et al: Antibiotic susceptibility testing by standardized single disc method. Am J Clin Path 45:493, 1966) utilized 30 mcg Augmentin® (AMC) discs for estimating the susceptibility of bacteria to Clavamox Tablets and Drops.

INDICATIONS AND USAGE

Clavamox Drops are indicated in the treatment of:
Dogs: Skin and soft tissue infections such as wounds, abscesses, cellulitis, superficial/juvenile and deep pyoderma due to susceptible strains of the following organisms: β-lactamase-producing Staphylococcus aureus, non-β-lactamase-producing Staphylococcus aureus, Staphylococcus spp., Streptococcus spp., and E. coli.

Peridontal infections due to susceptible strains of both aerobic and anaerobic bacteria. Clavamox has been shown to be clinically effective for treating cases of canine periodontal disease.

Cats: Skin and soft tissue infections such as wounds, abscesses, and cellulitis/dermatitis due to susceptible strains of the following organisms: β-lactamase-producing Staphylococcus aureus, non-β-lactamase-producing Staphylococcus aureus, Staphylococcus spp., Streptococcus spp., E. coli, Pasteurella multocida, and Pasteurella spp.

Urinary tract infections (cystitis) due to susceptible strains of E. coli.

Therapy may be initiated with Clavamox prior to obtaining results from bacteriological and susceptibility studies.

A culture should be obtained prior to treatment to determine susceptibility of the organisms to Clavamox. Following determination of susceptibility results and clinical response to medication, therapy may be reevaluated.

CONTRAINDICATIONS

The use of this drug is contraindicated in animals with a history of an allergic reaction to any of the penicillins or cephalosporins.

WARNINGS

Safety of use in pregnant or breeding animals has not been determined. For use in dogs and cats only.

ADVERSE REACTIONS

Clavamox contains a semisynthetic penicillin (amoxicillin) and has the potential for producing allergic reactions.

If an allergic reaction occurs, administer epinephrine and/or steroids.

DOSAGE AND ADMINISTRATION

Dogs: The recommended dosage is 6.25 mg/lb (1 mL/10 lb) of body weight twice a day. Skin and soft tissue infections such as abscesses, cellulitis, wounds, superficial/juvenile pyoderma, and periodontal infections should be treated for 5–7 days or for 48 hours after all symptoms have subsided. If no response is seen after 5 days of treatment, therapy should be discontinued and the case reevaluated. Deep pyoderma may require treatment for 21 days; the maximum duration of treatment should not exceed 30 days.

Cats: The recommended dosage is 62.5 mg (1 mL) twice a day. Skin and soft tissue infections such as abscesses and cellulitis/dermatitis should be treated for 5–7 days or 48 hours after all symptoms have subsided, not to exceed 30 days. If no response is seen after 3 days of treatment, therapy should be discontinued and the case reevaluated.

Urinary tract infections may require treatment for 10–14 days or longer. The maximum duration of treatment should not exceed 30 days.

Reconstitution instructions - Oral Suspension

Add 14 mL of water to the 15-mL bottle and shake vigorously. Each mL of suspension will contain 50 mg of amoxicillin activity as the trihydrate and 12.5 mg of clavulanic acid activity as the potassium salt.

Note: Any unused portion of the reconstituted suspension must be discarded after 10 days. Refrigeration of the reconstituted suspension is required.

HOW SUPPLIED

Clavamox Drops are supplied in 15-mL bottles containing 50 mg of amoxicillin/12.5 mg of clavulanic acid per mL.

Approved by FDA under NADA # 055-101

Clavamox is a trademark owned by and used under license from GlaxoSmithKline.

Augmentin is a trademark owned by GlaxoSmithKline.

zoetis

Distributed by:
Zoetis Inc.
Kalamazoo, MI 49007

Revised: February 2019

P1518388

PRINCIPAL DISPLAY PANEL - 15 mL Bottle Carton

CLAVAMOX®
(amoxicillin and clavulanate potassium for oral suspension), USP

Drops

For veterinary oral suspension

For use in dogs and cats

When reconstituted each mL contains 50 mg of amoxicillin USP as the trihydrate and 12.5 mg of clavulanic acid USP as the potassium salt.

Do Not Use if Product is Discolored

Caution: Federal law restricts this
drug to use by or on the order
of a licensed veterinarian.

15 mL

Approved by FDA under NADA # 055-101

zoetis